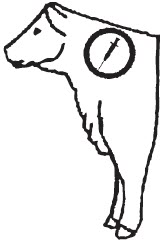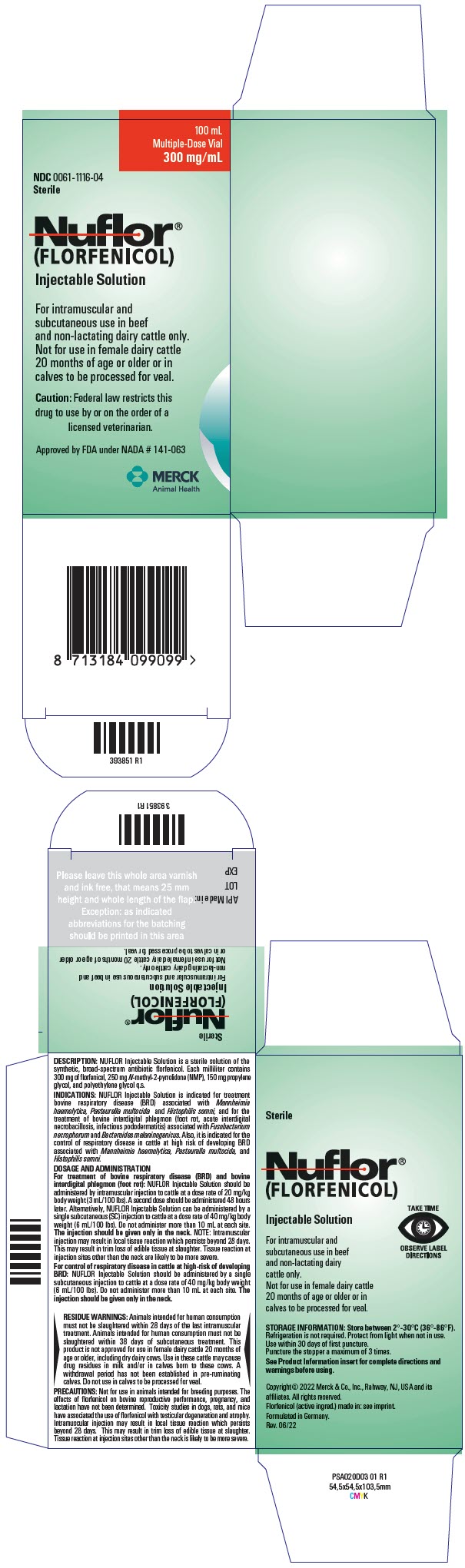 DRUG LABEL: Nuflor
NDC: 0061-1116 | Form: INJECTION, SOLUTION
Manufacturer: Merck Sharp & Dohme Corp.
Category: animal | Type: PRESCRIPTION ANIMAL DRUG LABEL
Date: 20241115

ACTIVE INGREDIENTS: FLORFENICOL 300 mg/1 mL

Nuflor®
(FLORFENICOL)
Injectable Solution
300 mg/mL

PRODUCT INFORMATION

Approved by FDA under NADA # 141-063

For intramuscular and subcutaneous use in beef and non-lactating dairy cattle only.

Not for use in female dairy cattle 20 months of age or older or in calves to be processed for veal.

SAFE HANDLING WARNING

CAUTION Federal law restricts this drug to use by or on the order of a licensed veterinarian.

DESCRIPTION

DESCRIPTION NUFLOR Injectable Solution is a solution of the synthetic antibiotic florfenicol. Each milliliter of sterile NUFLOR Injectable Solution contains 300 mg of florfenicol, 250 mg N-methyl-2-pyrrolidone (NMP), 150 mg propylene glycol, and polyeth-ylene glycol qs. The chemical name for florfenicol is 2,2-Dichloro-N-[1-(fluoromethyl)-2-hydroxy-2-[4-(methylsulfonyl)phenyl]ethyl] acetamide.

VETERINARY INDICATIONS

INDICATIONS NUFLOR Injectable Solution is indicated for treatment of bovine respiratory disease (BRD) associated with Mannheimia haemolytica, Pasteurella multocida, and Histophilus somni, and for the treatment of bovine interdigital phlegmon (foot rot, acute interdigital necrobacillosis, infectious pododermatitis) associated with Fusobacterium necrophorum and Bacteroides melaninogenicus. Also, it is indicated for the control of respiratory disease in cattle at high risk of developing BRD associated with Mannheimia haemolytica, Pasteurella multocida, and Histophilus somni.

DOSAGE AND ADMINISTRATION For treatment of bovine respiratory disease (BRD) and bovine interdigital phlegmon (foot rot): NUFLOR Injectable Solution should be administered by intramuscular injection to cattle at a dose rate of 20 mg/kg body weight (3 mL/100 lbs). A second dose should be adminis-tered 48 hours later. Alternatively, NUFLOR Injectable Solution can be administered by a single subcutaneous (SC) injection to cattle at a dose rate of 40 mg/kg body weight (6 mL/100 lbs). Do not administer more than 10 mL at each site. The injection should be given only in the neck.

NOTE: Intramuscular injection may result in local tissue reaction which persists beyond 28 days. This may result in trim loss of edible tissue at slaughter. Tissue reaction at injection sites other than the neck is likely to be more severe.

For control of respiratory disease in cattle at high-risk of developing BRD: NUFLOR Injectable Solution should be administered by a single subcutaneous injection to cattle at a dose rate of 40 mg/kg body weight (6 mL/100 lbs). Do not administer more than 10 mL at each site. The injection should be given only in the neck.

NUFLOR Injectable Solution DOSAGE GUIDE
ANIMAL WEIGHT (lbs) | IM NUFLOR DOSAGE 3.0 mL/100 lb Body Weight (mL) | SC NUFLOR DOSAGE 6.0 mL/100 lb Body Weight (mL) |  | Recommended Injection Location
100 | 3.0 | 6.0 |  | Recommended Injection Location
200 | 6.0 | 12.0 |  | Recommended Injection Location
300 | 9.0 | 18.0 |  | Recommended Injection Location
400 | 12.0 | 24.0 |  | Recommended Injection Location
500 | 15.0 | 30.0 |  | Recommended Injection Location
600 | 18.0 | 36.0 |  | Do not inject more than 10 mL per injection site.
700 | 21.0 | 42.0 |  | Do not inject more than 10 mL per injection site.
800 | 24.0 | 48.0 |  | Do not inject more than 10 mL per injection site.
900 | 27.0 | 54.0 |  | Do not inject more than 10 mL per injection site.
1000 | 30.0 | 60.0 |  | Do not inject more than 10 mL per injection site.

Clinical improvement should be evident in most treated subjects within 24 hours of initiation of treatment. If a positive response is not noted within 72 hours of initiation of treatment, the diagnosis should be re-evaluated.

CONTRAINDICATIONS

CONTRAINDICATIONS Do not use in animals that have shown hypersensitivity to florfenicol.

WARNINGS

USER SAFETY WARNINGS: NOT FOR HUMAN USE. KEEP OUT OF REACH OF CHILDREN. This product contains materials that can be irritating to skin and eyes. Avoid direct contact with skin, eyes, and clothing. In case of accidental eye exposure, flush with water for 15 minutes. In case of accidental skin exposure, wash with soap and water. Remove contaminated clothing. Consult a physician if irritation persists. Accidental injection of this product may cause local irritation. Consult a physician immediately. Reproductive and developmental toxicities have been reported in laboratory animals following high, repeated exposures to N-methyl-2-pyrrolidone (NMP). Pregnant women should wear gloves and exercise caution or avoid handling this product. The Safety Data Sheet (SDS) contains more detailed occupational safety information.

CONTACT INFORMATION: For customer service, adverse effects reporting and/or a copy of the SDS, call 1-800-211-3573. For additional information about adverse drug experience reporting for animal drugs, contact FDA at 1-888-FDA-VETS or www.fda.gov/reportanimalae.

PRECAUTIONS

PRECAUTIONS: Not for use in animals intended for breeding purposes. The effects of florfenicol on bovine reproductive performance, pregnancy, and lactation have not been determined. Toxicity studies in dogs, rats, and mice have associated the use of florfenicol with testicular degeneration and atrophy. Intramuscular injection may result in local tissue reaction which persists beyond 28 days. This may result in trim loss of edible tissue at slaughter. Tissue reaction at injection sites other than the neck is likely to be more severe.

RESIDUE WARNING

RESIDUE WARNINGS: Animals intended for human consumption must not be slaughtered within 28 days of the last intramuscular treatment. Animals intended for human consumption must not be slaughtered within 38 days of subcutaneous treatment. This product is not approved for use in female dairy cattle 20 months of age or older, including dry dairy cows. Use in these cattle may cause drug residues in milk and/or in calves born to these cows. A withdrawal period has not been established in pre-ruminating calves. Do not use in calves to be processed for veal.

ADVERSE REACTIONS

ADVERSE REACTIONS Inappetence, decreased water consumption, or diarrhea may occur transiently following treatment.

CLINICAL PHARMACOLOGY

CLINICAL PHARMACOLOGY The pharmacokinetic disposition of NUFLOR Injectable Solution was evaluated in feeder calves following single intramuscular (IM) administration at the recommended dose of 20 mg/kg body weight. NUFLOR Injectable Solution was also administered intravenously (IV) to the same cattle in order to calculate the volume of distribution, clearance, and percent bioavailability1 (Table 1).

TABLE 1. Pharmacokinetic Parameter Values for Florfenicol Following IM Administration of 20 mg/kg Body Weight to Feeder Calves (n=10).
Parameter | Median | Range
Cmax (μg/mL) | 3.07 [harmonic mean] | 1.43 - 5.60
tmax (hr) | 3.33 | 0.75 - 8.00
T ½ (hr) | 18.3 [mean value] | 8.30 - 44.0
AUC (μg∙min/mL) | 4242 | 3200 - 6250
Bioavailability (%) | 78.5 | 59.3 - 106
Vdss (L/kg) [following IV administration] | 0.77 | 0.68 - 0.85
Clt (mL/min/kg) | 3.75 | 3.17 - 4.31
Cmax Maximum serum concentration
Tmax Time at which Cmax is observed
T ½ Biological half-life
AUC Area under the curve
Vdss Volume of distribution at steady state
Clt Total body clearance

Florfenicol was detectable in the serum of most animals through 60 hours after intramuscular administration with a mean concentration of 0.19 μg/mL. The protein binding of flor-fenicol was 12.7%, 13.2%, and 18.3% at serum concentrations of 0.5, 3.0, and 16.0 μg/mL, respectively.

MICROBIOLOGY

MICROBIOLOGY Florfenicol is a synthetic, broad-spectrum antibiotic active against many Gram negative and Gram-positive bacteria isolated from domestic animals. It acts by binding to the 50S ribosomal subunit and inhibiting bacterial protein synthesis. Florfenicol is generally considered a bacteriostatic drug, but exhibits bactericidal activity against certain bacterial species. In vitro studies demonstrate that florfenicol is active against the bovine respiratory disease (BRD) pathogens Mannheimia haemolytica, Pasteurella multocida, and Histophilus somni, and that florfenicol exhibits bactericidal activity against strains of M. haemolytica and H. somni. Clinical studies confirm the efficacy of florfenicol against BRD as well as against commonly isolated bacterial pathogens in bovine inter-digital phlegmon including Fusobacterium necrophorum and Bacteroides melaninogenicus.

The minimum inhibitory concentrations (MICs) of florfenicol for BRD organisms were determined using isolates obtained from natural infections from 1990 to 1993. The MICs for interdigital phlegmon organisms were determined using isolates obtained from natural infections from 1973 to 1997 (Table 2).

TABLE 2. Florfenicol Minimum Inhibitory Concentration (MIC) Values [The correlation between the in vitro susceptibility data and clinical effectiveness is unknown.] of Indicated Pathogens Isolated From Natural Infections of Cattle.
Indicated pathogens | Year of isolation | Isolate Numbers | MIC50 [The lowest MIC to encompass 50% and 90% of the most susceptible isolates, respectively.] (μg/mL) | MIC90 (μg/mL)
Mannheimia haemolytica | 1990 to 1993 | 398 | 0.5 | 1
Pasteurella multocida | 1990 to 1993 | 350 | 0.5 | 0.5
Histophilis somni | 1990 to 1993 | 66 | 0.25 | 0.5
Fusobacterium necrophorum | 1973 to 1997 | 33 | 0.25 | 0.25
Bacteroides melaninogenicus | 1973 to 1997 | 20 | 0.25 | 0.25

ANIMAL SAFETY A 10× safety study was conducted in feeder calves. Two intramuscular injections of 200 mg/kg were administered at a 48-hour interval. The calves were monitored for 14 days after the second dose. Marked anorexia, decreased water consumption, decreased body weight, and increased serum enzymes were observed following dose administration. These effects resolved by the end of the study.

A 1×, 3×, and 5× (20, 60, and 100 mg/kg) safety study was conducted in feeder calves for 3× the duration of treatment (6 injections at 48-hour intervals). Slight decrease in feed and water consumption was observed in the 1× dose group. Decreased feed and water consumption, body weight, urine pH, and increased serum enzymes, were observed in the 3× and 5× dose groups. Depression, soft stool consistency, and dehydration were also observed in some animals (most fre-quently at the 3× and 5× dose levels), primarily near the end of dosing.

A 43-day controlled study was conducted in healthy cattle to evaluate effects of NUFLOR Injectable Solution administered at the recommended dose on feed consumption. Although a tran-sient decrease in feed consumption was observed, NUFLOR Injectable Solution administration had no long-term effect on body weight, rate of gain, or feed consumption.

STORAGE AND HANDLING

STORAGE INFORMATION Store between 2°-30°C (36°-86°F). Refrigeration is not required. Protect from light when not in use. Use within 30 days of first puncture. For the 100mL vials, puncture the stopper a maximum of 3 times. For the 250mL and 500mL vials, puncture the stopper a maximum of 17 times.

HOW SUPPLIED

HOW SUPPLIED NUFLOR Injectable Solution is packaged in 100 mL (NDC 0061-1116-04), 250 mL (NDC 0061-1116-05), and 500 mL (NDC 0061-1116-06) glass sterile multiple-dose vials.

REFERENCES

REFERENCE 1. Lobell RD, Varma KJ, et al. Pharmacokinetics of florfenicol following intravenous and intramuscular doses to cattle. J Vet Pharmacol Therap. 1994;17:253-258.

Copyright© 2022 Merck & Co., Inc., Rahway, NJ, USA and its affiliates. All rights reserved.

Formulated in Germany.

Rev. 06/22

394942 R1

PRINCIPAL DISPLAY PANEL - 100 mL Vial Carton

100 mL
Multiple-Dose Vial
300 mg/mL

NDC 0061-1116-04
Sterile

Nuflor®
(FLORFENICOL)
Injectable Solution

For intramuscular and
subcutaneous use in beef
and non-lactating dairy cattle only.
Not for use in female dairy cattle
20 months of age or older or in
calves to be processed for veal.

Caution: Federal law restricts this
drug to use by or on the order of a
licensed veterinarian.

Approved by FDA under NADA # 141-063

MERCK
Animal Health